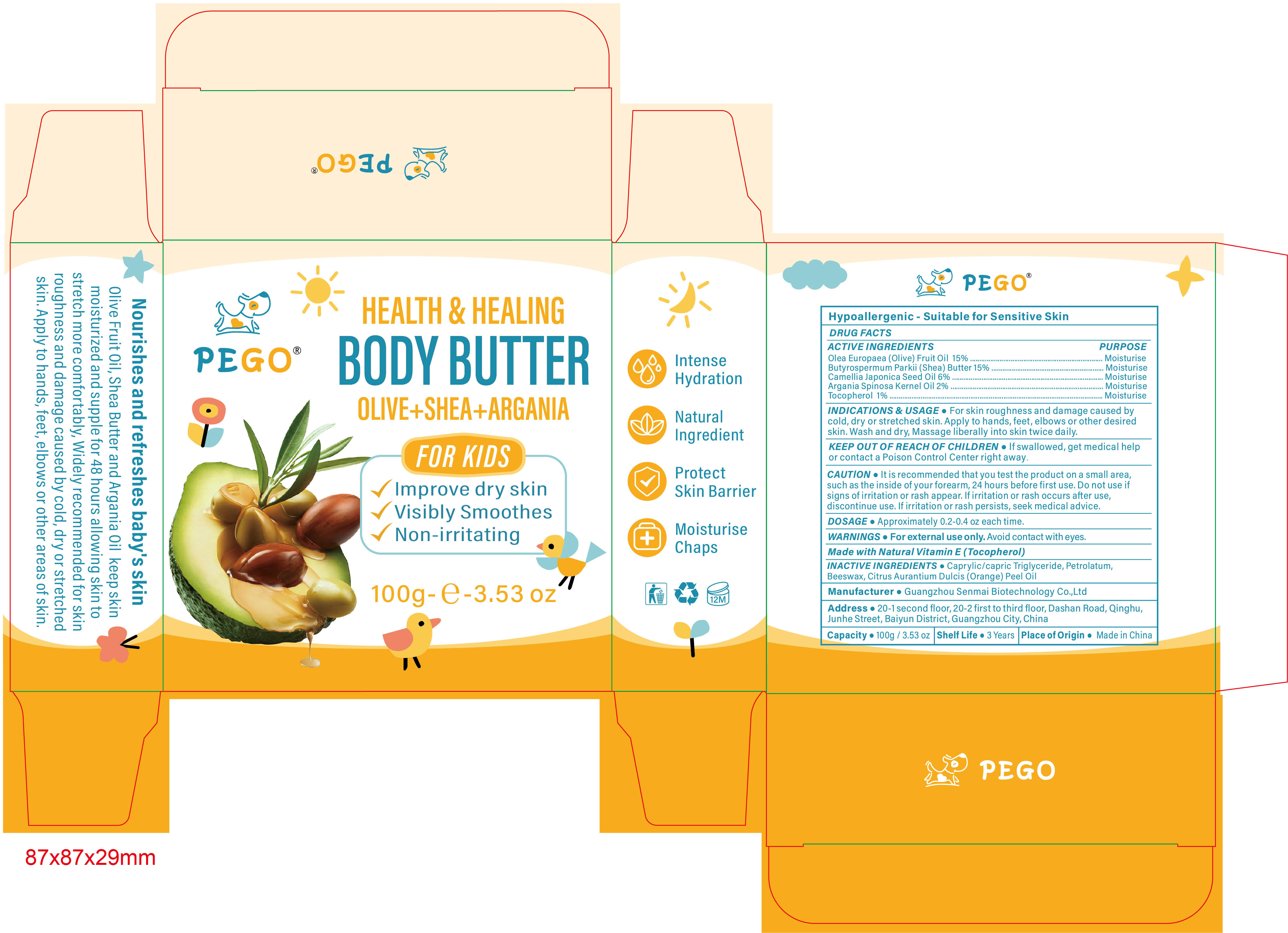 DRUG LABEL: PEGO BODY BUTTER FOR KIDS
NDC: 84509-024 | Form: CREAM
Manufacturer: Guangzhou Senmai Biotechnology Co.,Ltd
Category: otc | Type: HUMAN OTC DRUG LABEL
Date: 20241015

ACTIVE INGREDIENTS: OLIVE OIL 15000 mg/100 g; CAMELLIA JAPONICA SEED OIL 6000 mg/100 g; ARGAN OIL 2000 mg/100 g; TOCOPHEROL 1000 mg/100 g; SHEA BUTTER 15000 mg/100 g
INACTIVE INGREDIENTS: YELLOW WAX; PETROLATUM; MEDIUM-CHAIN TRIGLYCERIDES; ORANGE OIL

Active Ingredients

Olea Europaea (Olive) Fruit Oil 15%

Butyrospermum Parkii (Shea) Butter 15%

Camellia Japonica Seed Oil 6%

Argania Spinosa Kernel Oil 2%

Tocopherol 1%

Purpose

Moisturise

Inactive Ingredients

Caprylic/capric Triglyceride, Petrolatum, Beeswax, Citrus Aurantium Dulcis (Orange) Peel Oil

DOSAGE

Approximately 0.2-0.4 oz each time

Warnings

For external use only. Avoid contact with eyes.

Uses

For skin roughness and damage caused by cold, dry or stretched skin. Apply to hands, feet, elbows or other desired skin. Wash and dry, Massage liberally into skin twice daily.

Keep out of reach of children

If swallowed, get medical help or contact a Poison Control Center right away.

CAUTION

It is recommended that you test the product on a small area, such as the inside of your forearm, 24 hours before first use. Do not use if signs of irritation or rash appear. If irritation or rash occurs after use, discontinue use. If irritation or rash persists, seek medical advice.

DESCRIPTION

Made with Natural Vitamin E (Tocopherol)

Product Name

PEGO BODY BUTTER FOR KIDS

Manufacturer

Guangzhou Senmai Biotechnology Co.,Ltd

Address

20-1 second floor, 20-2 first to third floor, Dashan Road, Qinghu, Junhe Street, Baiyun District, Guangzhou City, China

Capacity

100g/3.53oz

Shelf Life

3 Years

Place of Origin

Made in China